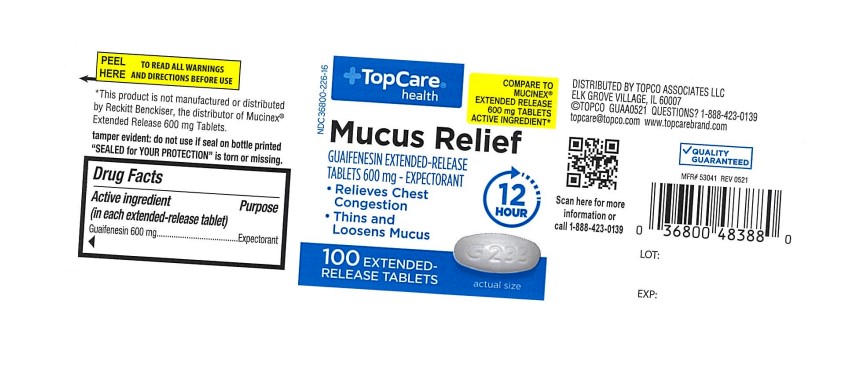 DRUG LABEL: Topco Mucus Relief
NDC: 36800-226 | Form: TABLET, EXTENDED RELEASE
Manufacturer: Topco Associates, LLC
Category: otc | Type: Human OTC Drug Label
Date: 20251203

ACTIVE INGREDIENTS: GUAIFENESIN 600 mg/1 1
INACTIVE INGREDIENTS: CARBOMER HOMOPOLYMER, UNSPECIFIED TYPE; HYPROMELLOSE, UNSPECIFIED; CELLULOSE, MICROCRYSTALLINE; POVIDONE

Topcare health Mucus Relief
Guaifenesin Extended-Release Tablets 600 mg

ACTIVE INGREDIENT(in each extended-release tablet)

Guaifenesin 600 mg

PURPOSE

Expectorant

USE(S)

helps loosen phlegm (mucus) and thin bronchial secretions to rid the bronchial passageways of bothersome mucus and make coughs more productive

WARNING

.

DO NOT USE

for children under 12 years of age

ASK A DOCTOR BEFORE USE IF YOU HAVE

- persistent or chronic cough such as occurs with smoking, asthma, chronic bronchitis, or emphysema
- cough accompanied by too much phlegm (mucus)

STOP USE AND ASK A DOCTOR IF

- cough lasts more than 7 days, comes back, or occurs with fever, rash, or persistent headache. These could be signs of a serious illness.

IF PREGNANT OR BREAST-FEEDING,

ask a health professional before use.

KEEP OUT OF REACH OF CHILDREN

In case of overdose, get medical help or contact a Poison Control Center right away (1-800-222-1222).

DIRECTIONS

- do not crush, chew, or break tablet
- take with a full glass of water
- this product can be administered without regard for the timing of meals
- adults and children 12 years of age and over: 1 or 2 tablets every 12 hours. Do not exceed 4 tablets in 24 hours.
- children under 12 years of age: do not use

OTHER INFORMATION

- tamper evident: do not use if seal on bottle printed "SEALED for YOUR PROTECTION" is torn or missing
- store between 20 to 25°C (68 to 77°F)

INACTIVE INGREDIENTS

carbomer homopolymer, hypromellose, microcrystalline cellulose, povidone

QUESTIONS?

1-609-860-2600

Hours: 8am - 4pm, EST

You may also report side effects to this phone number.

PRINCIPAL DISPLAY PANEL

Topcare health

NDC 36800-226-16

COMPARE TO MUCINEX® EXTENDED RELEASE TABLETS 600 mg - EXPECTORANT

Mucus Relief

GUAIFENESIN EXTENDED RELEASE TABLETS 600 mg - EXPECTORANT

- Relieves Chest Congestion
- Thins and Loosens Mucus

12 Hour

100 EXTENDED-RELEASE TABLETS